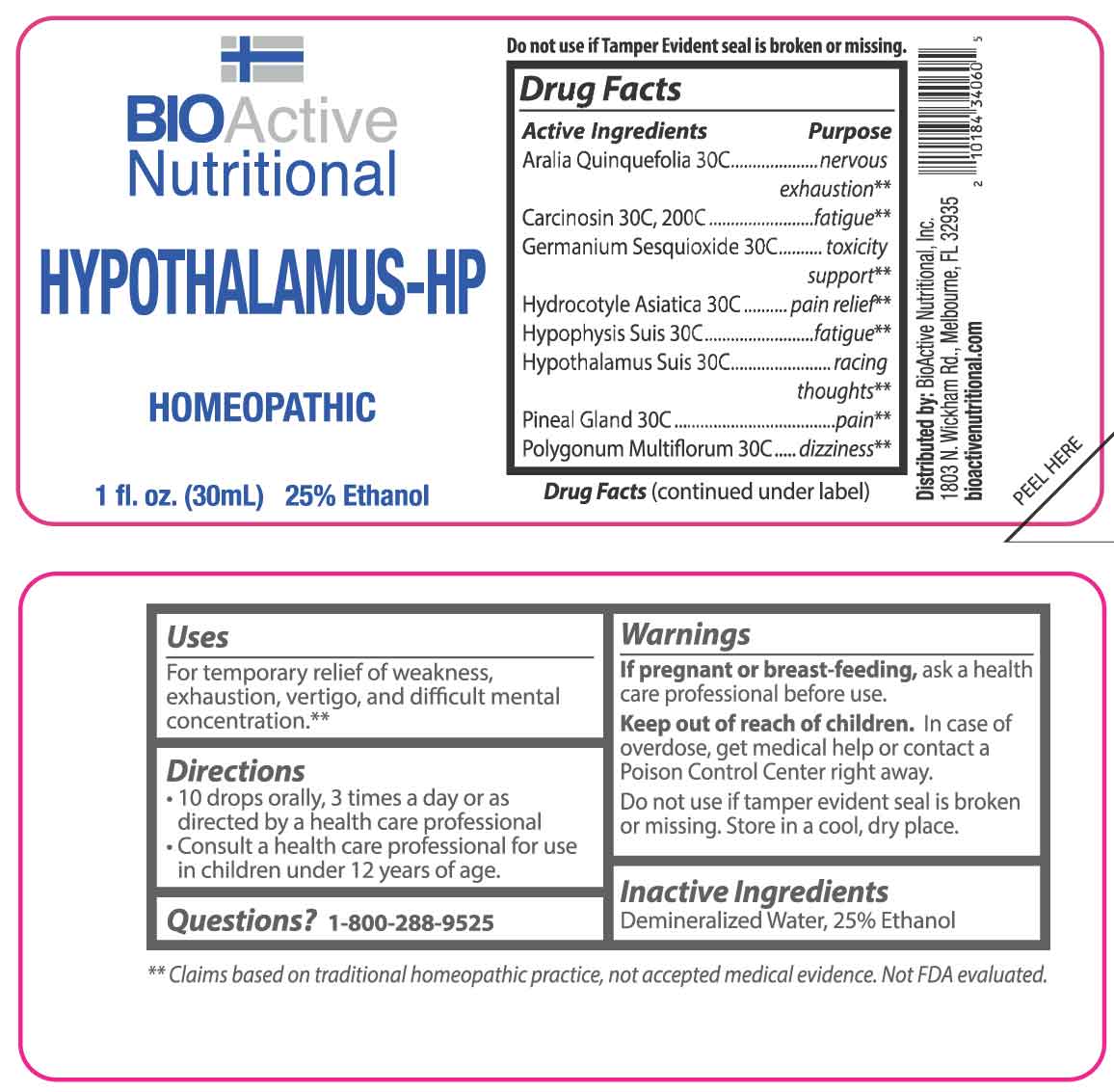 DRUG LABEL: Hypothalamus
NDC: 43857-0063 | Form: LIQUID
Manufacturer: BioActive Nutritional, Inc.
Category: homeopathic | Type: HUMAN OTC DRUG LABEL
Date: 20251215

ACTIVE INGREDIENTS: AMERICAN GINSENG 30 [hp_C]/1 mL; GERMANIUM SESQUIOXIDE 30 [hp_C]/1 mL; CENTELLA ASIATICA WHOLE 30 [hp_C]/1 mL; SUS SCROFA HYPOTHALAMUS 30 [hp_C]/1 mL; SUS SCROFA PINEAL GLAND 30 [hp_C]/1 mL; SUS SCROFA PITUITARY GLAND 30 [hp_C]/1 mL; FALLOPIA MULTIFLORA ROOT 30 [hp_C]/1 mL; HUMAN BREAST TUMOR CELL 30 [hp_C]/1 mL
INACTIVE INGREDIENTS: WATER; ALCOHOL

DRUG FACTS:

ACTIVE INGREDIENTS:

Aralia Quinquefolia 30C, Carcinosin 30C, 200C, Germanium Sesquioxide 30C, Hydrocotyle Asiatica 30C, Hypophysis Suis 30C, Hypothalamus Suis 30C, Pineal Gland (Suis) 30C, Polygonum Multiflorum 30C.

PURPOSE:

Aralia Quinquefolia – nervous exhaustion,** Carcinosin - fatigue,** Germanium Sesquioxide – toxicity support,** Hydrocotyle Asiatica – pain relief,** Hypophysis Suis - fatigue,** Hypothalamus Suis – racing thoughts,** Pineal Gland - pain,** Polygonum Multiflorum – dizziness**

**Claims based on traditional homeopathic practice, not accepted medical evidence. Not FDA evaluated.

USES:

For temporary relief of weakness, exhaustion, vertigo, and difficult mental concentration.**

**Claims based on traditional homeopathic practice, not accepted medical evidence. Not FDA evaluated.

WARNINGS:

If pregnant or breast-feeding, ask a health care professional before use.

Keep out of reach of children. In case of overdose, get medical help or contact a Poison Control Center right away.

Do not use if tamper evident seal is broken or missing.

Store in a cool, dry place.

KEEP OUT OF REACH OF CHILDREN:

In case of overdose, get medical help or contact a Poison Control Center right away.

DIRECTIONS:

• 10 drops orally, 3 times a day or as directed by a health care professional.

• Consult a health care professional for use in children under 12 years of age.

INACTIVE INGREDIENTS:

Demineralized Water, 25% Ethanol

QUESTIONS:

Distributed by:
BioActive Nutritional, Inc.
1803 N. Wickham Rd.
Melbourne, FL 32935
bioactivenutritional.com

1-800-288-9525

PACKAGE LABEL DISPLAY:

BIOActive Nutritional
HYPOTHALAMUS-HP
HOMEOPATHIC
1 fl. oz. (30 mL)